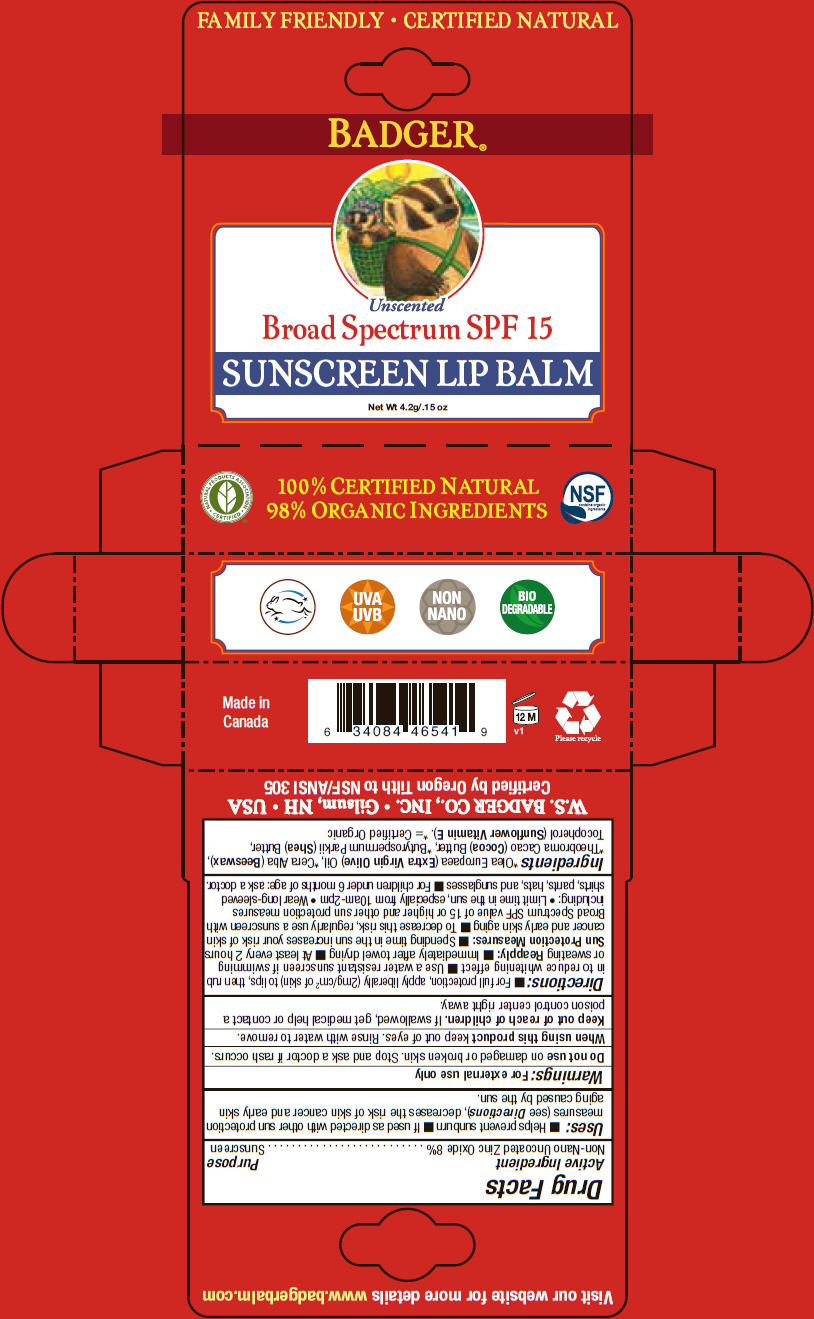 DRUG LABEL: Badger SPF 15 Sunscreen Lip Balm
NDC: 55143-108 | Form: STICK
Manufacturer: Norwood Packaging Ltd.
Category: otc | Type: HUMAN OTC DRUG LABEL
Date: 20140115

ACTIVE INGREDIENTS: ZINC OXIDE 8 g/100 g
INACTIVE INGREDIENTS: OLIVE OIL; YELLOW WAX; COCOA BUTTER; SHEA BUTTER; TOCOPHEROL

Badger® SPF 15 Sunscreen Lip Balm

Drug Facts

Active Ingredient

Non-Nano Uncoated Zinc Oxide 8%

Purpose

Sunscreen

Uses

- Helps prevent sunburn
- If used as directed with other sun protection measures (see Directions), decreases the risk of skin cancer and early skin aging caused by the sun.

Warnings

For external use only

Do not use on damaged or broken skin. Stop and ask a doctor if rash occurs.

When using this product keep out of eyes. Rinse with water to remove.

Keep out of reach of children. If swallowed, get medical help or contact a poison control center right away.

Directions

- For full protection, apply liberally (2mg/cm^2 of skin) to lips, then rub in to reduce whitening effect
- Use a water resistant sunscreen if swimming or sweating

Reapply:

- Immediately after towel drying
- At least every 2 hours

Sun Protection Measures:

- Spending time in the sun increases your risk of skin cancer and early skin aging
- To decrease this risk, regularly use a sunscreen with Broad Spectrum SPF value of 15 or higher and other sun protection measures including:
  - Limit time in the sun, especially from 10am-2pm
  - Wear long-sleeved shirts, pants, hats, and sunglasses
- For children under 6 months of age: ask a doctor.

Ingredients

[= Certified Organic] Olea Europaea (Extra Virgin Olive) Oil, Cera Alba (Beeswax), Theobroma Cacao (Cocoa) Butter, Butyrospermum Parkii (Shea) Butter, Tocopherol (Sunflower Vitamin E).

PRINCIPAL DISPLAY PANEL - 4.2 g Tube Box

FAMILY FRIENDLY • CERTIFIED NATURAL

BADGER®

Unscented

Broad Spectrum SPF 15

SUNSCREEN LIP BALM

Net Wt 4.2g/.15 oz

UVA
UVB

NON
NANO

BIO
DEGRADABLE